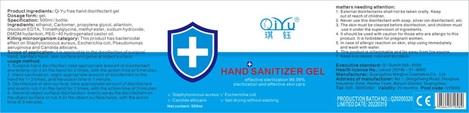 DRUG LABEL: Qi Yu free hand disinfectant gel
NDC: 74447-012 | Form: LIQUID
Manufacturer: Guangzhou Minghui Cosmetics Co., Ltd.
Category: otc | Type: HUMAN OTC DRUG LABEL
Date: 20200619

ACTIVE INGREDIENTS: ALCOHOL 375 mL/500 mL
INACTIVE INGREDIENTS: ALLANTOIN; DMDM HYDANTOIN; PROPYLENE GLYCOL; CARBOXYPOLYMETHYLENE; WATER; EDETATE SODIUM; POLYOXYL 40 HYDROGENATED CASTOR OIL; BETAINE; SODIUM HYDROXIDE; MONOMETHYL ADIPATE

Qi Yu free hand disinfectant gel

ACTIVE INGREDIENT

Alcohol 75 % v/v

PURPOSE

Antiseptic

INDICATIONS AND USAGE

Hand Sanitizer to help reduce bacteria that potentially can cause disease. For use when soap and water are not available.

WARNINGS

For external use only. Flammable. Keep away from heat or flame

DO NOT USE

- In children less than 2 months of age
- On open skin wounds

Stop use and ask a doctor if irritation or rash occurs. These may be signs of a serious condition.

Keep out of reach of children. If swallowed, get medical help or contact a poison control center right away.

Directions:

- Place enough product on hands to cover all surfaces. Rub hands together until dry.
- Supervise children under 6 years of age when using this product to avoid swallowing.

Other Information:

Store between 15-30c (59-86F)

Avoid freezing and excessive heat above 40 C (104F)

INACTIVE INGREDIENT

Inactive ingredients CARBOXYPOLYMETHYLENE, Propylene glycol, Allantoin, EDETATE SODIUM, BETAINE, MONOMETHYL ADIPATE, Sodium hydroxide, DMDM Hydantoin, PEG-40 hydrogenated castor oil, water

Qi Yu free hand disinfectant gel 500mL

74447-012-01